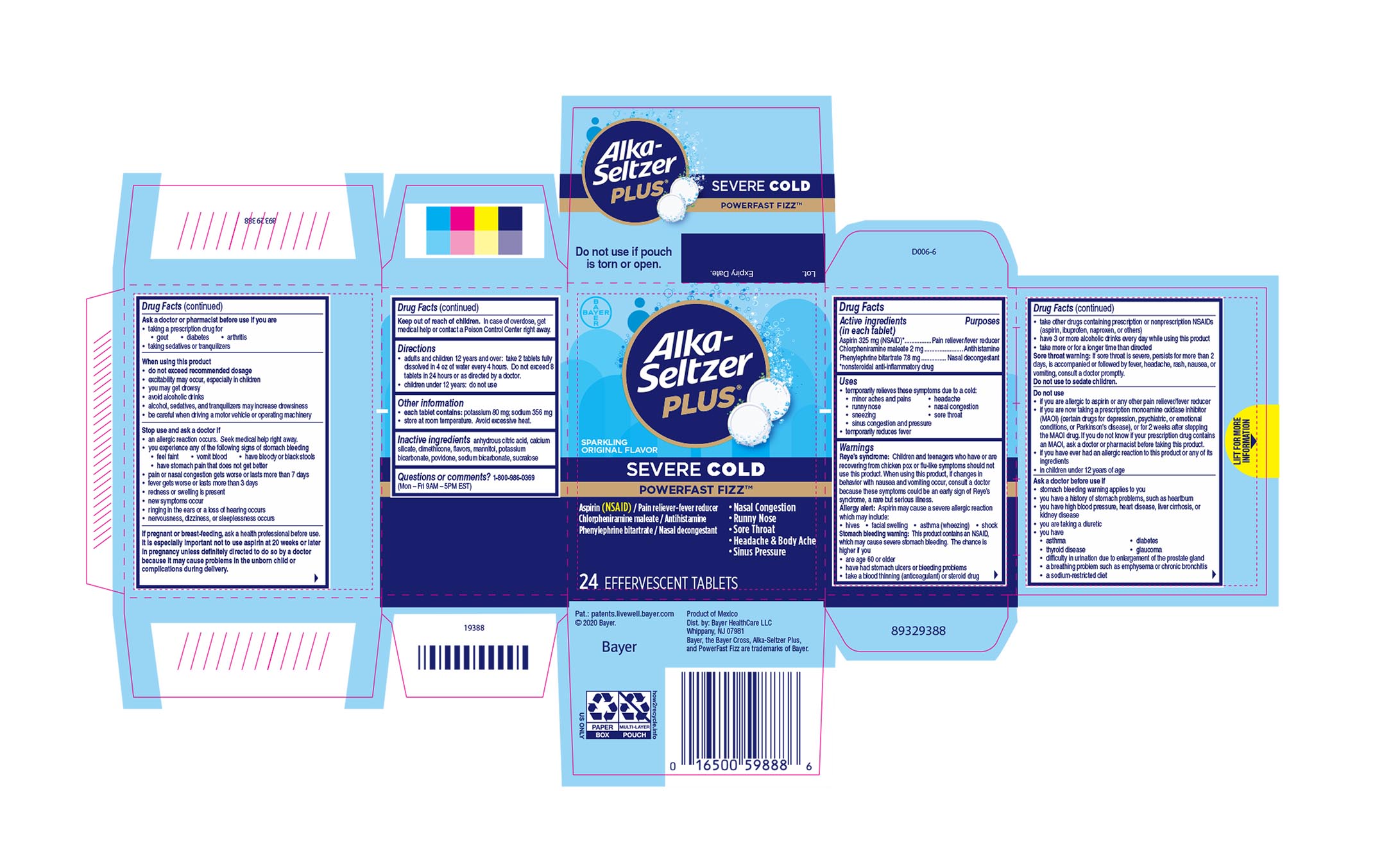 DRUG LABEL: Alka-Seltzer Plus Cold Sparkling Original PowerFast Fizz
NDC: 0280-0060 | Form: TABLET, EFFERVESCENT
Manufacturer: Bayer HealthCare LLC.
Category: otc | Type: HUMAN OTC DRUG LABEL
Date: 20251204

ACTIVE INGREDIENTS: ASPIRIN 325 mg/1 1; CHLORPHENIRAMINE MALEATE 2 mg/1 1; PHENYLEPHRINE BITARTRATE 7.8 mg/1 1
INACTIVE INGREDIENTS: DIMETHICONE; POTASSIUM BICARBONATE; SUCRALOSE; ANHYDROUS CITRIC ACID; CALCIUM SILICATE; MANNITOL; SODIUM BICARBONATE; POVIDONE

ASP Severe Cold Sparkling Original PowerFast Fizz UI1614456

Drug Facts

Active ingredients (in each tablet) Purposes

Aspirin 325 mg (NSAID)*…..………….……..Pain reliever/fever reducer

Chlorpheniramine maleate 2 mg.……………..…...…….....Antihistamine

Phenylephrine bitartrate 7.8 mg …........…………...Nasal decongestant

*nonsteroidal anti-inflammatory drug

Uses

temporarily relieves these symptoms due to a cold:

- minor aches and pains
- headache
- runny nose
- nasal congestion
- sneezing
- sore throat
- sinus congestion and pressure

temporarily reduces fever

WARNINGS

Reye’s syndrome: Children and teenagers who have or are recovering from chicken pox or flu-like symptoms should not use this product. When using this product, if changes in behavior with nausea and vomiting occur, consult a doctor because these symptoms could be an early sign of Reye’s syndrome, a rare but serious illness.

Allergy alert

Allergy alert: Aspirin may cause a severe allergic reaction which may include:

● hives

● facial swelling

● asthma (wheezing)

● shock

Stomach bleeding warning: This product contains an NSAID, which may cause severe stomach bleeding. The chance is higher if you

● are age 60 or older

● have had stomach ulcers or bleeding problems

● take a blood thinning (anticoagulant) or steroid drug

● take other drugs containing prescription or nonprescription NSAIDs (aspirin, ibuprofen, naproxen, or others)

● have 3 or more alcoholic drinks every day while using this product

● take more or for a longer time than directed

Sore throat warning: If sore throat is severe, persists for more than 2 days, is accompanied or followed by fever, headache, rash, nausea, or vomiting, consult a doctor promptly.

Do not use to sedate children.

Do not use

● if you are allergic to aspirin or any other pain reliever/fever reducer

● if you are now taking a prescription monoamine oxidase inhibitor (MAOI) (certain drugs for depression, psychiatric, or emotional

conditions, or Parkinson's disease), or for 2 weeks after stopping the MAOI drug. If you do not know if your prescription drug contains an MAOI, ask a doctor or pharmacist before taking this product.

● if you have ever had an allergic reaction to this product or any of its ingredients

● in children under 12 years of age

Ask a doctor before use if

● stomach bleeding warning applies to you

● you have a history of stomach problems, such as heartburn

● you have high blood pressure, heart disease, liver cirrhosis, or kidney disease

● you are taking a diuretic

● you have

● asthma

● diabetes

● thyroid disease

● glaucoma

● difficulty in urination due to enlargement of the prostate gland

● a breathing problem such as emphysema or chronic bronchitis

● a sodium-restricted diet

Ask a doctor or pharmacist before use if you are

taking a prescription drug for

- gout
- diabetes
- arthritis

taking sedatives or tranquilizers

Ask a doctor or pharmacist before use if you are

taking a prescription drug for

- gout
- diabetes
- arthritis

taking sedatives or tranquilizers

PREGNANCY OR BREAST FEEDING

If pregnant or breast-feeding, ask a health professional before use.

It is especially important not to use aspirin at 20 weeks or later in pregnancy unless definitely directed to do so by a doctor because it may cause problems in the unborn child or complications during delivery.

Keep out of reach of children. In case of overdose, get medical help or contact a Poison Control Center right away.

Directions

● adults and children 12 years and over: take 2 tablets fully dissolved in 4 oz of water every 4 hours. Do not exceed 8 tablets in 24 hours or as directed by a doctor.

● children under 12 years: do not use

Other information
● each tablet contains: potassium 80 mg; sodium 356 mg

● store at room temperature. Avoid excessive heat.

INACTIVE INGREDIENT

Inactive ingredients anhydrous citric acid, calcium silicate, dimethicone, flavors, mannitol, potassium bicarbonate, povidone, sodium bicarbonate, sucralose

Questions or comments? 1-800-986-0369 (Mon – Fri 9AM – 5PM EST)

PACKAGE LABEL

Alka-Seltzer Plus®

Severe Cold

Sparkling Original

POWERFAST FIZZ™

NEW LESS RESIDUE

ASPIRIN (NSAID)/Pain Reliever-Fever Reducer

Chlorpheniramine Maleate/Antihistamine

Phenylephrine Bitartrate/Nasal Decongestant

- Nasal Congestion
- Runny Nose
- Sore Throat
- Headache + Body Ache
- Sinus Pressure

24 EFFERVESCENT TABLETS